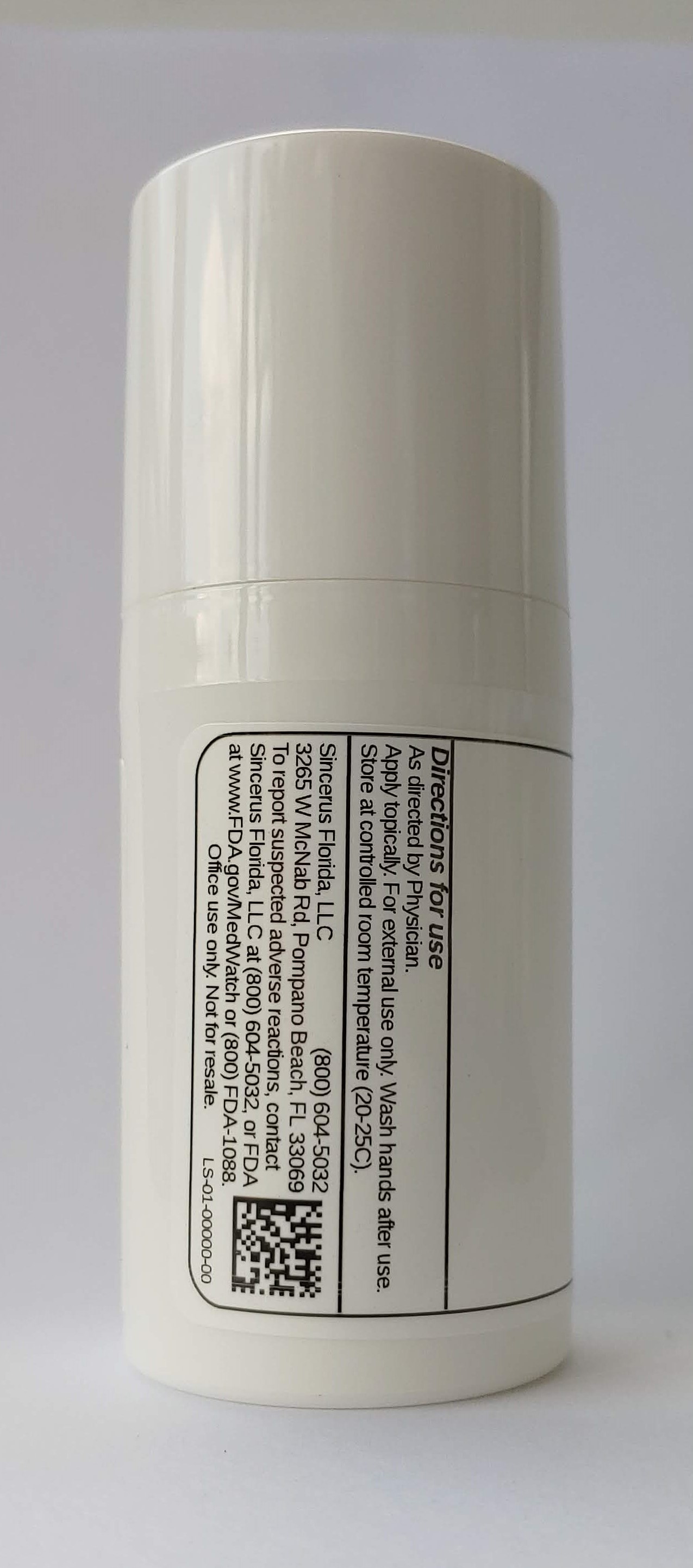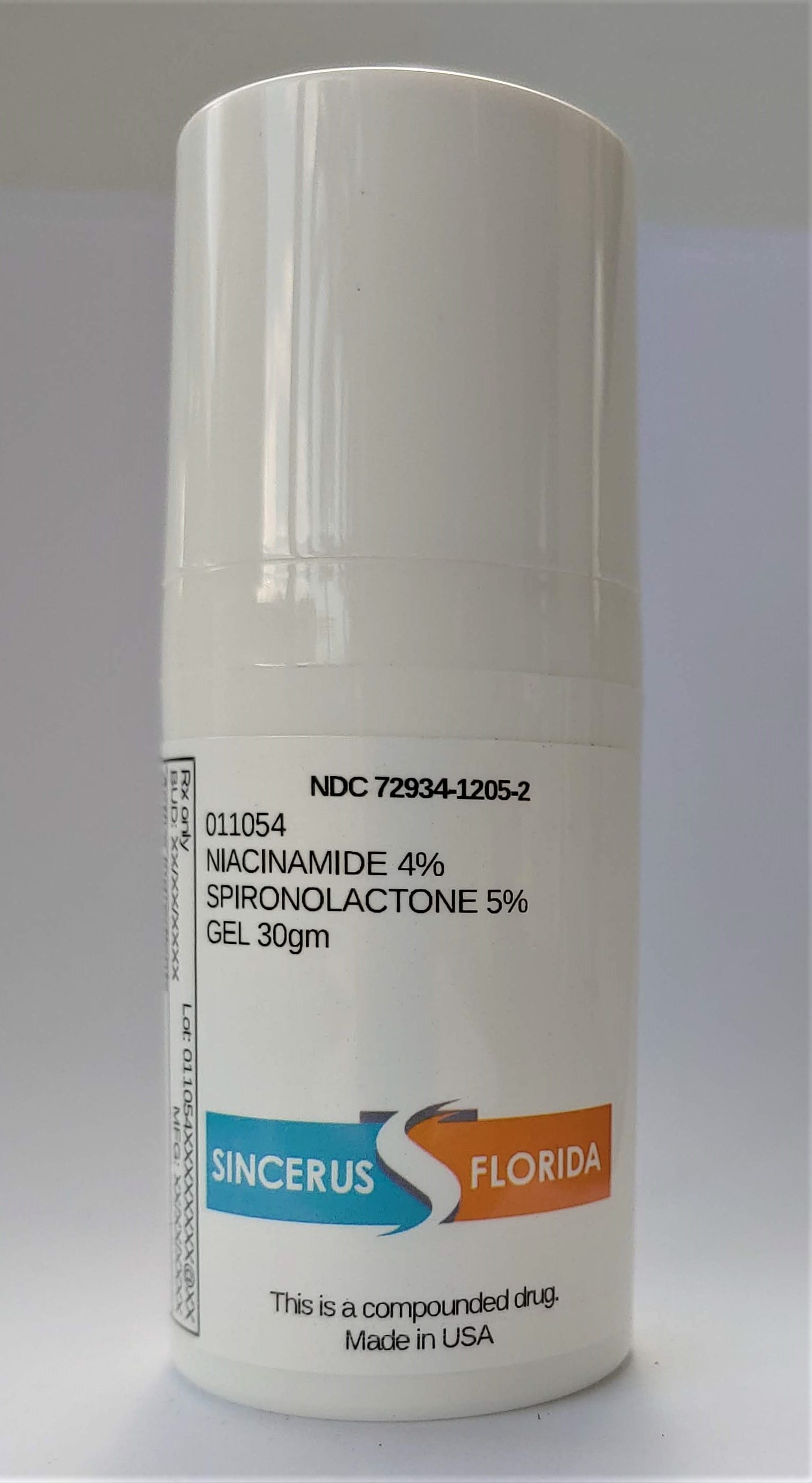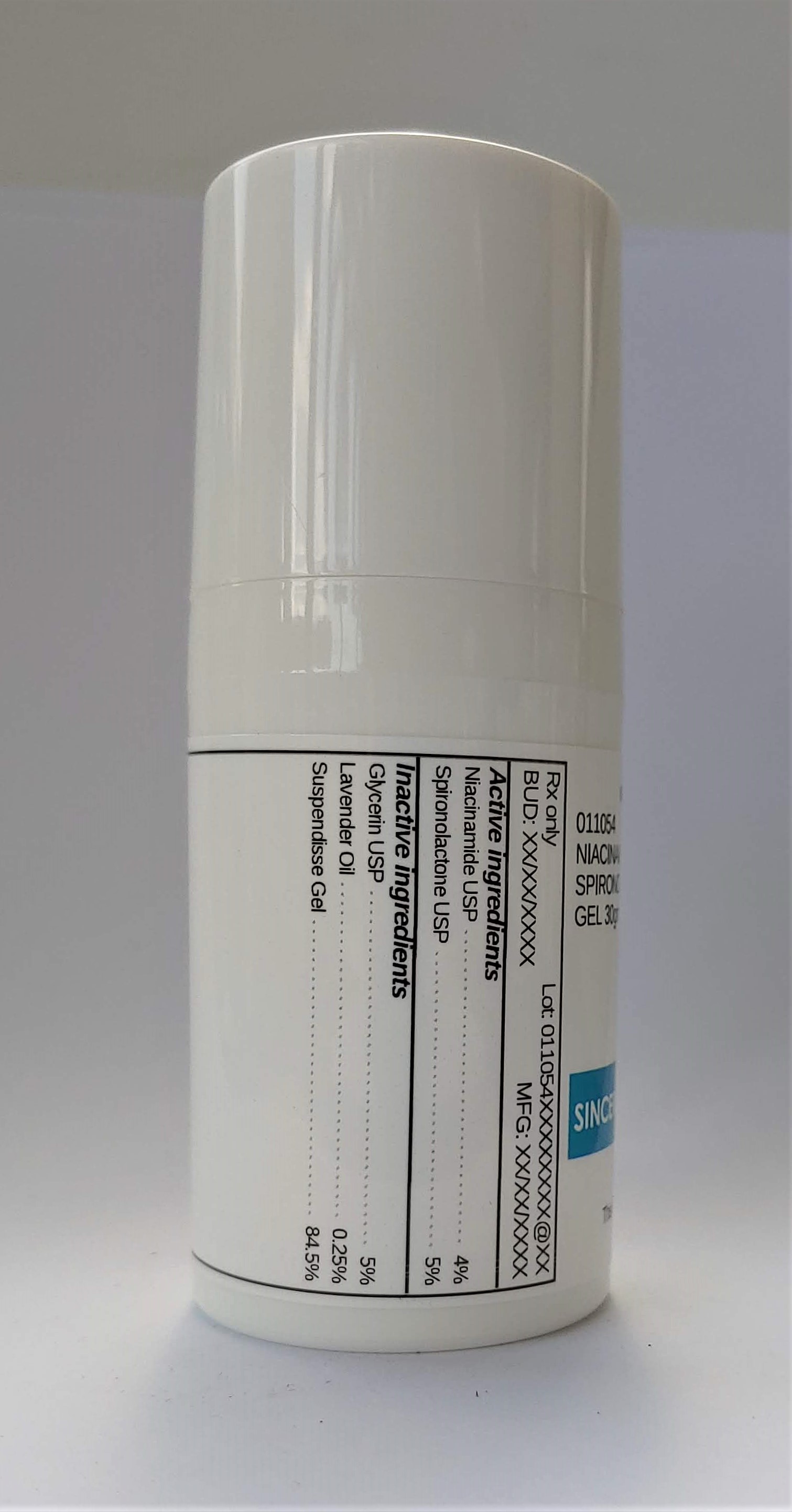 DRUG LABEL: 011054 NIACINAMIDE 4% / SPIRONOLACTONE 5%
NDC: 72934-1205 | Form: GEL
Manufacturer: Sincerus Florida, LLC
Category: prescription | Type: HUMAN PRESCRIPTION DRUG LABEL
Date: 20200702

ACTIVE INGREDIENTS: NIACINAMIDE 4 g/100 g; SPIRONOLACTONE 5 g/100 g

011054 NIACINAMIDE 4% / SPIRONOLACTONE 5%